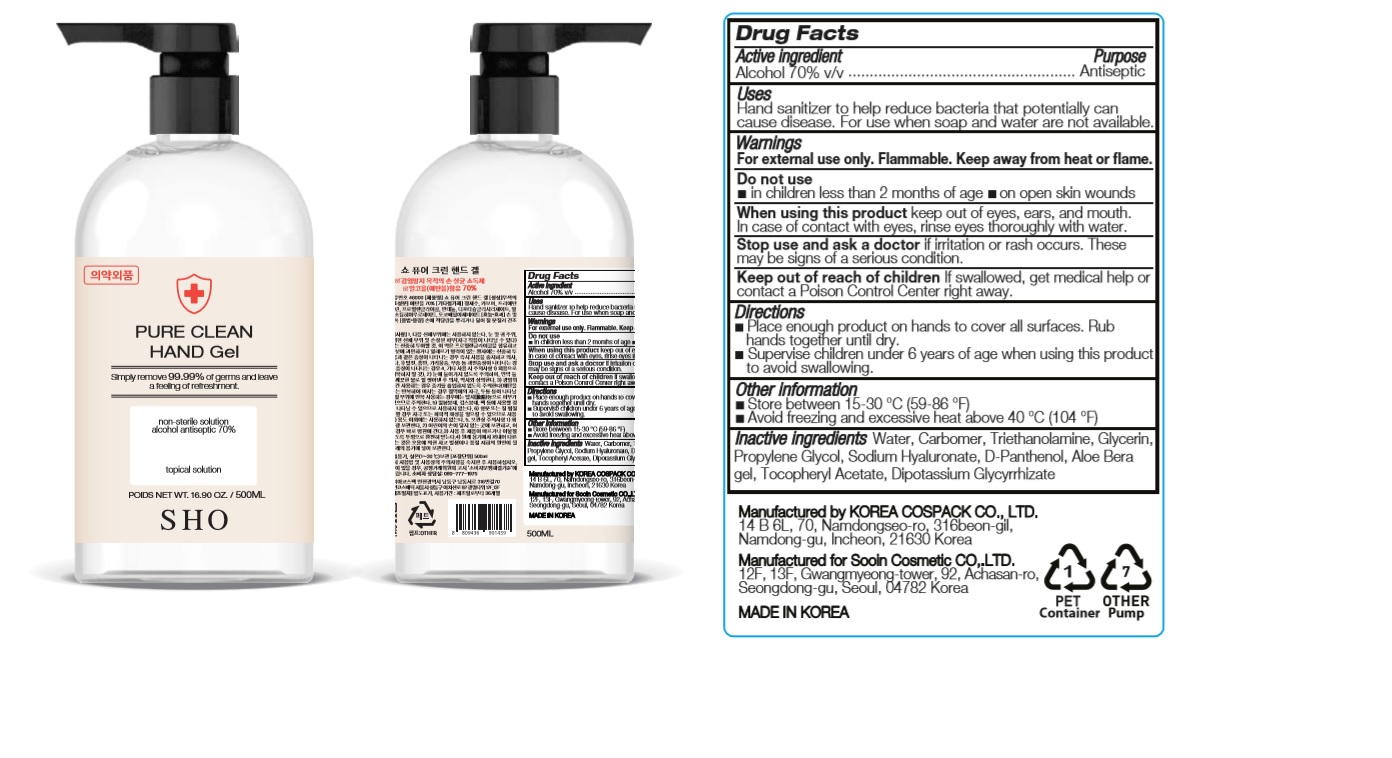 DRUG LABEL: PURE CLEAN HAND Gel
NDC: 74064-2570 | Form: GEL
Manufacturer: KOREA COSPACK CO.,LTD.
Category: otc | Type: HUMAN OTC DRUG LABEL
Date: 20200402

ACTIVE INGREDIENTS: ALCOHOL 350 mL/500 mL
INACTIVE INGREDIENTS: TROLAMINE; PROPYLENE GLYCOL; GLYCERIN; GLYCYRRHIZINATE DIPOTASSIUM; WATER; DEXPANTHENOL; HYALURONATE SODIUM; ALOE VERA LEAF; CARBOMER HOMOPOLYMER, UNSPECIFIED TYPE; .ALPHA.-TOCOPHEROL ACETATE

PURE CLEAN HAND Gel 500 ml : 74064-2570